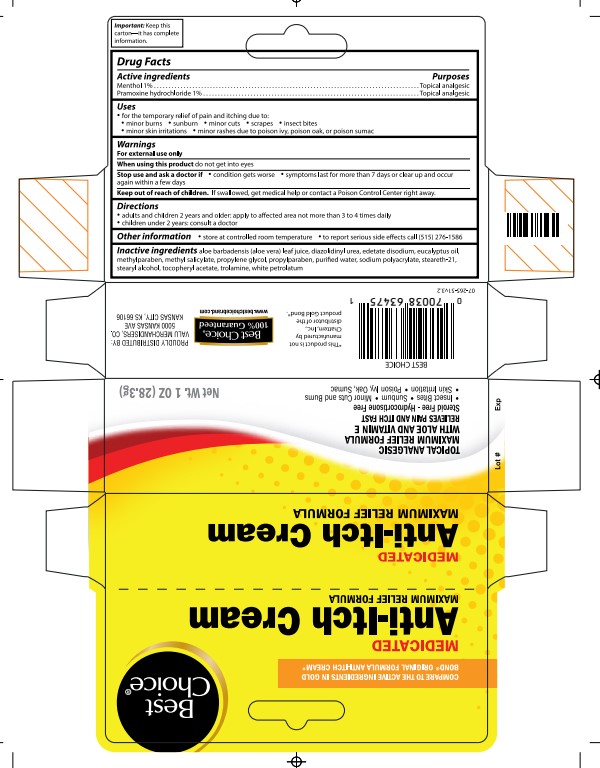 DRUG LABEL: Best Choice Medicated anti itch
NDC: 63941-265 | Form: CREAM
Manufacturer: value merchandisers
Category: otc | Type: HUMAN OTC DRUG LABEL
Date: 20231212

ACTIVE INGREDIENTS: PRAMOXINE HYDROCHLORIDE 1 g/100 g; MENTHOL 1 g/100 g
INACTIVE INGREDIENTS: PROPYLPARABEN; STEARETH-21; .ALPHA.-TOCOPHEROL ACETATE, DL-; SODIUM POLYACRYLATE (8000 MW); EDETATE DISODIUM; TROLAMINE; PROPYLENE GLYCOL; METHYL SALICYLATE; ALOE VERA LEAF; WATER; PETROLATUM; STEARYL ALCOHOL; METHYLPARABEN; EUCALYPTUS OIL; DIAZOLIDINYL UREA

Best Choice Medicated Anti itch Cream

Active Ingredient

Menthol 1%

Pramoxine hydrochloride 1%

Uses

for the temporary relief of pain and itching due to: minor burns, sunburn, minor cuts, scrapes, insect bites, minor skin irritations ,minor rashes due to poison ivy, poison oak, or poison sumac

Purpose

Topical anagesic

Warnings

When using this product

do not get into eyes

Keep out of reach of children

If swallowed, get medical help or contact a Poison Control Center right away.

Other Information

store at controlled room temperature

Directions

adults and children 2 years and older: apply to affected area not more than 3 to 4 times daily

children under 2 years: consult a doctor

DOSAGE AND ADMINISTRATION

Adults and Children 2 years and older: Apply to affected are not more than 3 to 4 times daily.

Inactive Ingredients

aloe barbadensis (aloe vera) leaf juice, diazolidinyl urea, edetate disodium, eucalyptus oil, methylparaben, methyl salicylate, mineral oil, PPG-1 trideceth-6, propylene glycol, propylparaben, purified water, sodium acrylates copolymer, steareth-21, stearyl alcohol, tocopheryl acetate, trolamine, white petrolatum

package principal panel

Health Best Choice Care

Maximum Relief with Aloe and Vitamin E

Relieves Pain and Itch Fast

Steroid Free- Hydrocortisone Free